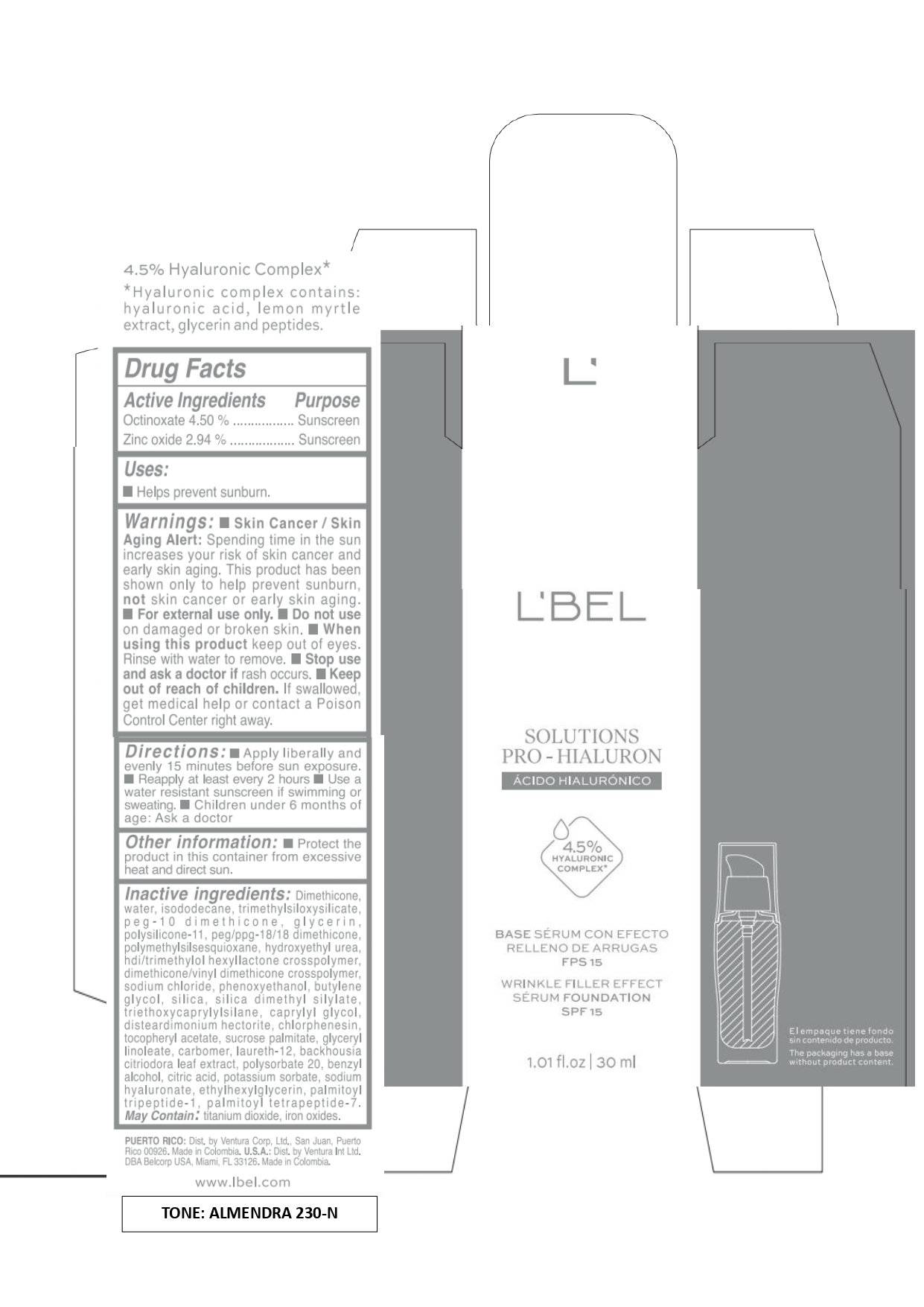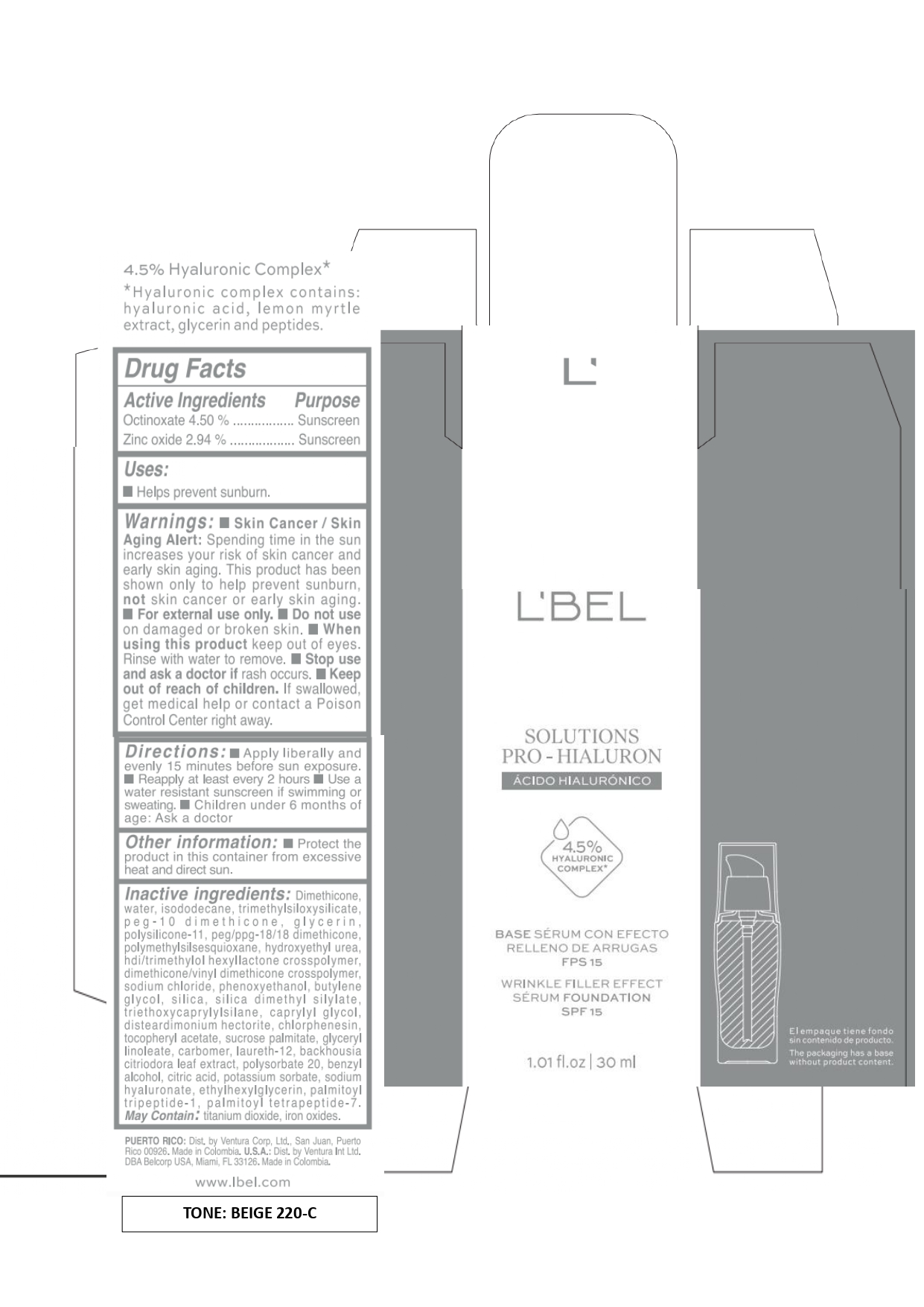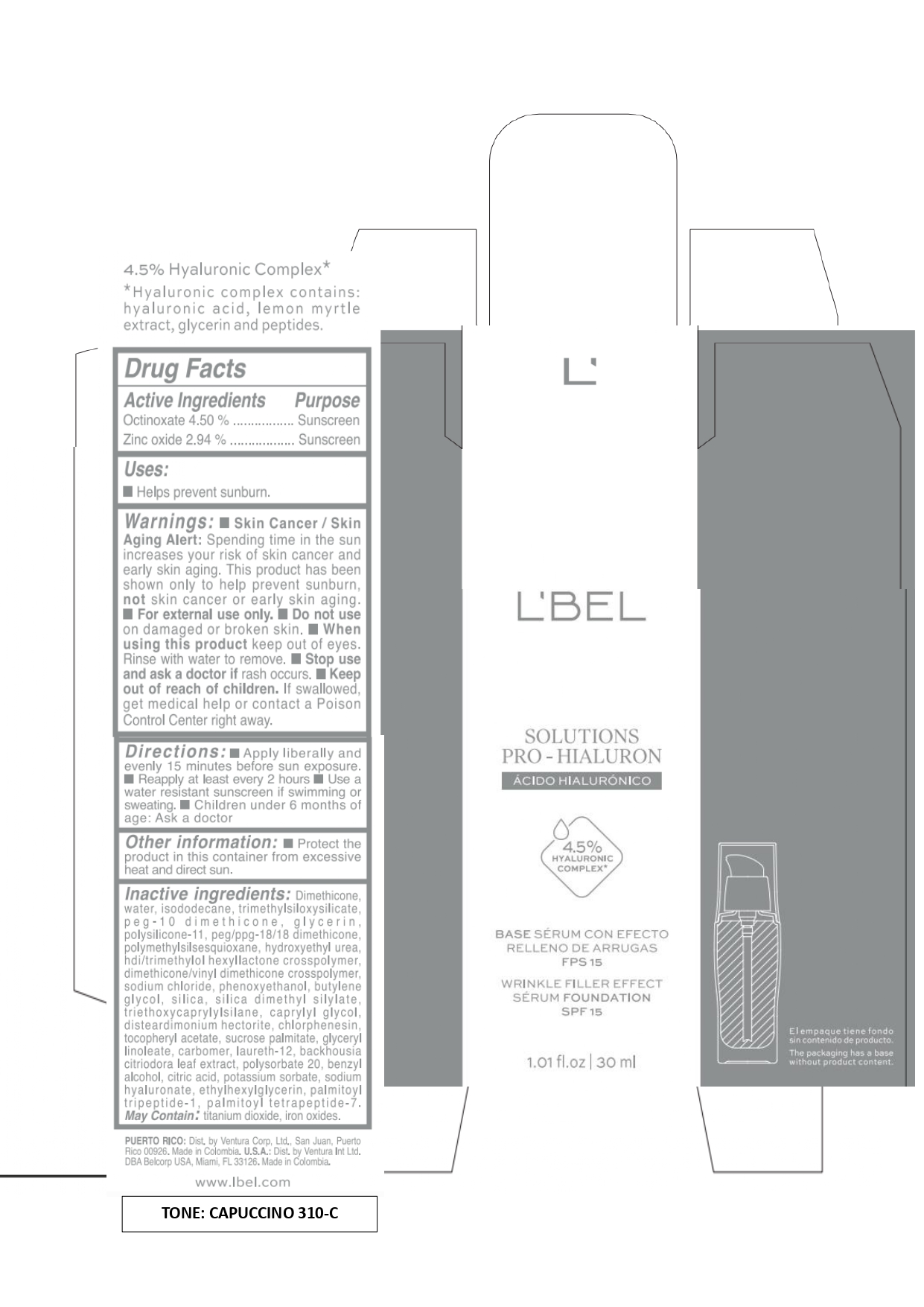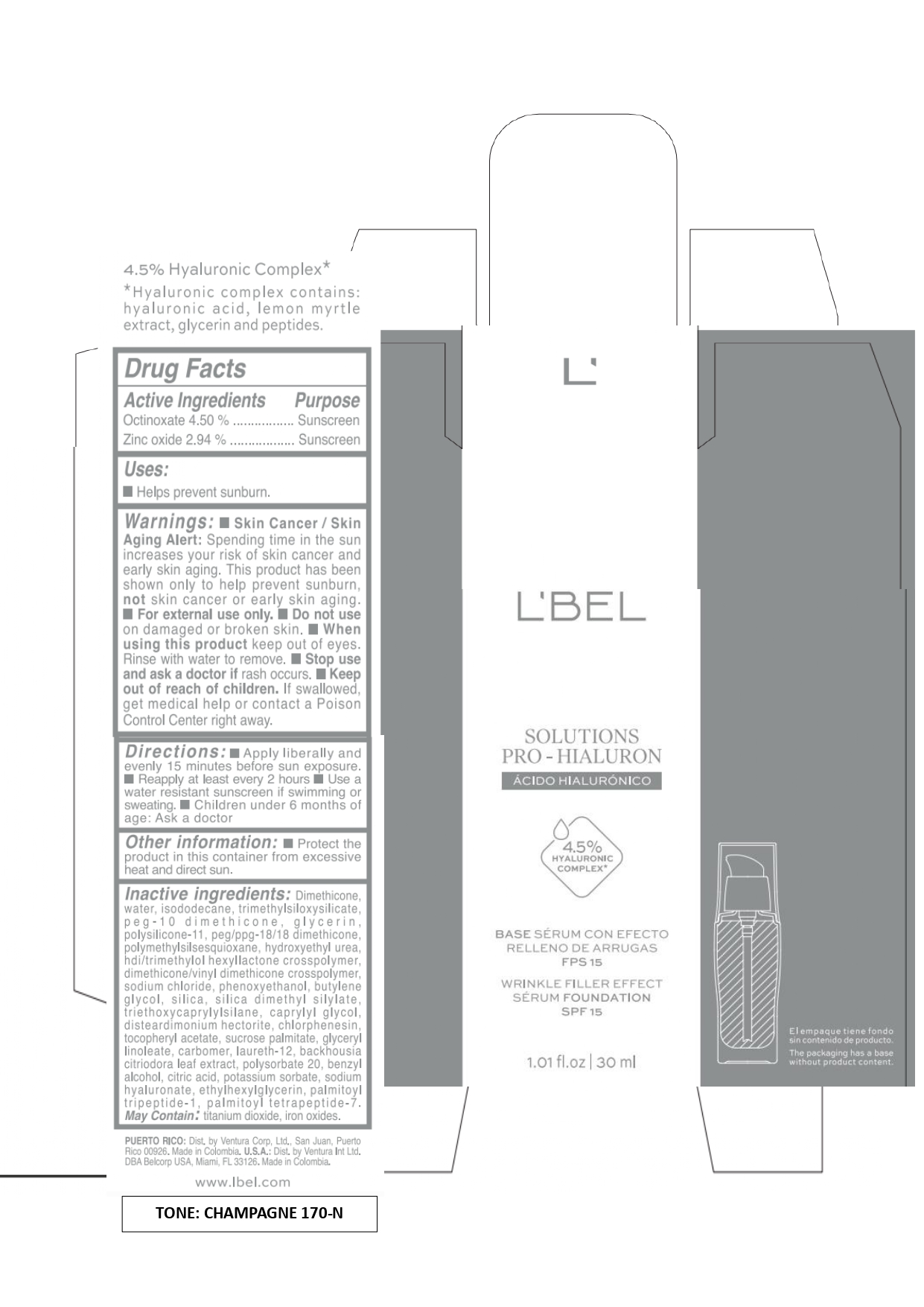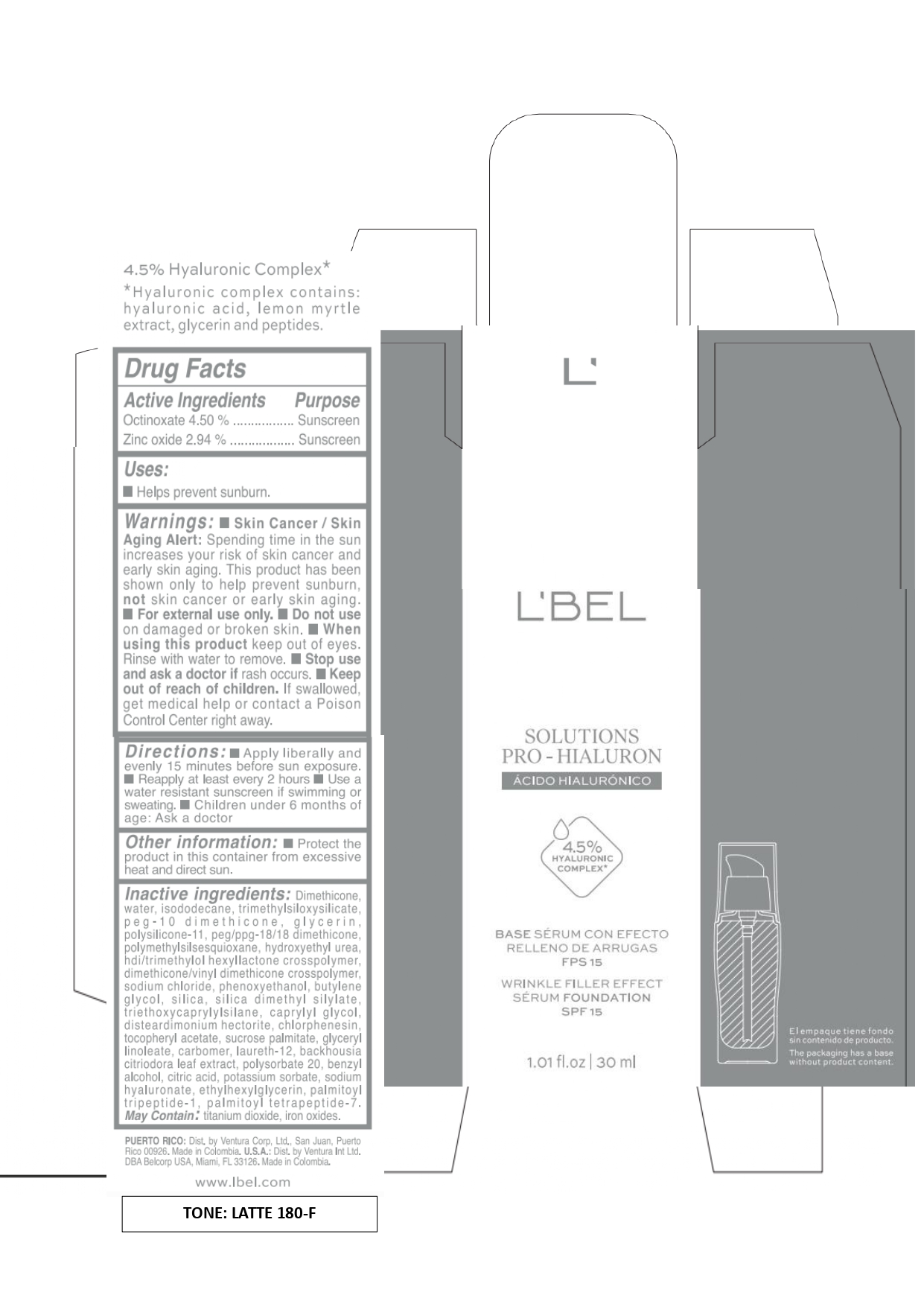 DRUG LABEL: LBEL SOLUTIONS PRO-HIALURON BASE SERUM CON EFECTO RELLENO DE ARRUGAS FPS 15 WRINKLE FILLER EFFECT SERUM FOUNDATION SPF 15 CAPUCCINO 310-C
NDC: 14141-337 | Form: LIQUID
Manufacturer: BEL STAR S.A.
Category: otc | Type: HUMAN OTC DRUG LABEL
Date: 20241028

ACTIVE INGREDIENTS: ZINC OXIDE 29.4 mg/1 mL; OCTINOXATE 45 mg/1 mL
INACTIVE INGREDIENTS: HYDROXYETHYL UREA; FERRIC OXIDE RED; LAURETH-12; BACKHOUSIA CITRIODORA LEAF; CITRIC ACID MONOHYDRATE; DIMETHICONE; PEG-10 DIMETHICONE (600 CST); DIMETHICONE/VINYL DIMETHICONE CROSSPOLYMER (SOFT PARTICLE); HEXAMETHYLENE DIISOCYANATE/TRIMETHYLOL HEXYLLACTONE CROSSPOLYMER; PALMITOYL TETRAPEPTIDE-7; ISODODECANE; GLYCERIN; TRIMETHYLSILOXYSILICATE (M/Q 0.6-0.8); .ALPHA.-TOCOPHEROL ACETATE; TRIETHOXYCAPRYLYLSILANE; CARBOMER HOMOPOLYMER, UNSPECIFIED TYPE; SODIUM CHLORIDE; POLYSORBATE 20; HYALURONATE SODIUM; DIMETHICONE/VINYL DIMETHICONE CROSSPOLYMER (HARD PARTICLE); PHENOXYETHANOL; DISTEARDIMONIUM HECTORITE; SUCROSE PALMITATE; SILICA DIMETHYL SILYLATE; CAPRYLYL GLYCOL; PEG/PPG-18/18 DIMETHICONE; FERRIC OXIDE YELLOW; WATER; SILICON DIOXIDE; GLYCERYL LINOLEATE; TITANIUM DIOXIDE; PALMITOYL TRIPEPTIDE-1; BUTYLENE GLYCOL; BENZYL ALCOHOL; FERROSOFERRIC OXIDE; POTASSIUM SORBATE; ETHYLHEXYLGLYCERIN; CHLORPHENESIN; POLYMETHYLSILSESQUIOXANE (4.5 MICRONS)

L'BEL SOLUTIONS PRO-HIALURON BASE SERUM CON EFECTO RELLENO DE ARRUGAS FPS 15 WRINKLE FILLER EFFECT SERUM FOUNDATION SPF 15

Active Ingredients

Octinoxate 4.50%

Zinc oxide 2.94%

Purpose

Sunscreen

Uses

- Helps prevent sunburn.

Warnings

- Skin Cancer/Skin Aging Alert: Spending time in the sun increases your risk of skin cancer and early skin aging. This product has been shown only to hep prevent sunburn, not skin cancer or early skin aging.
- For external use only.

Do not use

on damaged or broken skin.

When using this product

keep out of eyes. Rinse with water to remove.

Stop use and ask a doctor if

rash occurs.

Keep out of reach of children.

If swallowed, get medical help or contact a Poison Control Center right away.

Directions

- Apply liberally and evenly 15 minutes before sun exposure.
- Reapply at least every 2 hours
- Use a water resistant sunscreen if swimming or sweating.
- Children under 6 months of age: Ask a doctor

Other information

- Protect the product in this container from excessive heat and direct sun.

Inactive ingredients

Dimethicone, water, isododecane, trimethylsiloxysilicate, peg-10 dimethicone, glycerin, polysilicone-11, peg/ppg-18/18 dimethicone, polymethylsilsesquioxane, hydroxyethyl urea, hdi/trimethylol hexyllactone crosspolymer, dimethicone/vinyl dimethicone crosspolymer, sodium chloride, phenoxyethano, butylene glycol, silica, silica dimethyl silylate, triethoxycaprylylsilane, caprylyl glycol, disteardimonium hectorite, chlorphenesin, tocopheryl acetate, sucrose palmitate, glyceryl linoleate, carbomer, laureth-12, backhousia citriodora leaf extract, polysorbate 20, benzyl alcohol, citric acid, potassium sorbate, sodium hyaluronate, ethylhexylglycerin, palmitoyl tripeptide-1, palmitoyl tetrapeptide-7.

May Contain: titanium dioxide, iron oxides.